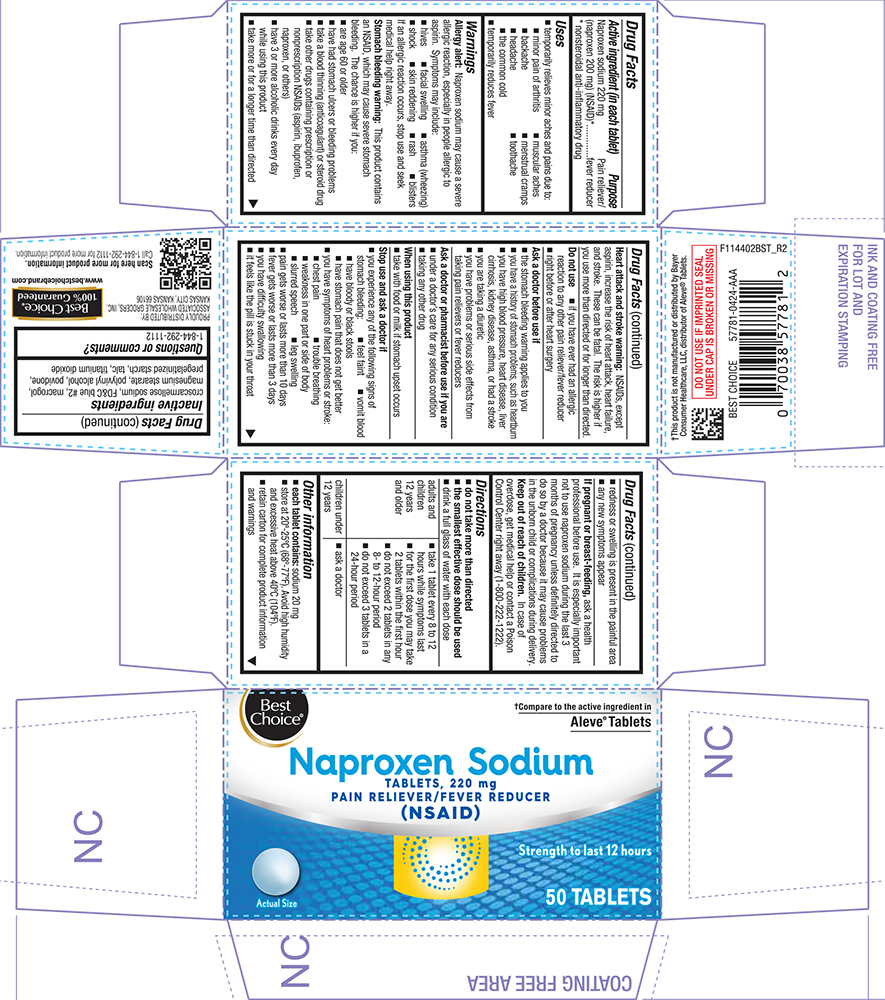 DRUG LABEL: Naproxen Sodium
NDC: 63941-444 | Form: TABLET, COATED
Manufacturer: VALU MERCHANDISERS COMPANY
Category: otc | Type: HUMAN OTC DRUG LABEL
Date: 20251211

ACTIVE INGREDIENTS: NAPROXEN SODIUM 220 mg/1 1
INACTIVE INGREDIENTS: CROSCARMELLOSE SODIUM; FD&C BLUE NO. 2; POLYETHYLENE GLYCOL, UNSPECIFIED; MAGNESIUM STEARATE; POLYVINYL ALCOHOL; POVIDONE, UNSPECIFIED; STARCH, CORN; TALC; TITANIUM DIOXIDE

1144-BST-2024-0613

Drug Facts

Active ingredient (in each tablet)

Naproxen sodium 220 mg (naproxen 200 mg) (NSAID [nonsteroidal anti-inflammatory drug])

Purpose

Pain reliever/fever reducer

Uses

- temporarily relieves minor aches and pains due to:
  - minor pain of arthritis
  - muscular aches
  - backache
  - menstrual cramps
  - headache
  - toothache
  - the common cold
- temporarily reduces fever

Warnings

Allergy alert

Naproxen sodium may cause a severe allergic reaction, especially in people allergic to aspirin. Symptoms may include:

- hives
- facial swelling
- asthma (wheezing)
- shock
- skin reddening
- rash
- blisters

If an allergic reaction occurs, stop use and seek medical help right away.

Stomach bleeding warning

This product contains an NSAID, which may cause severe stomach bleeding. The chance is higher if you:

- are age 60 or older
- have had stomach ulcers or bleeding problems
- take a blood thinning (anticoagulant) or steroid drug
- take other drugs containing prescription or nonprescription NSAIDs (aspirin, ibuprofen, naproxen, or others)
- have 3 or more alcoholic drinks every day while using this product
- take more or for a longer time than directed

Do not use

- if you have ever had an allergic reaction to any other pain reliever/fever reducer
- right before or after heart surgery

Ask a doctor before use if

- stomach bleeding warning applies to you
- you have a history of stomach problems, such as heartburn
- you have high blood pressure, heart disease, liver cirrhosis, or kidney disease
- you are taking a diuretic
- you have asthma
- you have problems or serious side effects from taking pain relievers or fever reducers

Ask a doctor or pharmacist before use if you are

- under a doctor's care for any serious condition
- taking any other drug

When using this product

- take with food or milk if stomach upset occurs
- long term continuous use may increase the risk of heart attack or stroke

Stop use and ask a doctor if

- side effects occur. You may report side effects to FDA at 1-800-FDA-1088.
- you experience any of the following signs of stomach bleeding:
  - feel faint
  - vomit blood
  - have bloody or black stools
  - have stomach pain that does not get better
- pain gets worse or lasts more than 10 days
- fever gets worse or lasts more than 3 days
- you have difficulty swallowing
- it feels like the pill is stuck in your throat
- you develop heartburn
- redness or swelling is present in the painful area
- any new symptoms appear

PREGNANCY OR BREAST FEEDING

If pregnant or breast-feeding,ask a health professional before use. It is especially important not to use naproxen sodium during the last 3 months of pregnancy unless definitely directed to do so by a doctor because it may cause problems in the unborn child or complications during delivery.

Keep out of reach of children.In case of overdose, get medical help or contact a Poison Control Center right away.

Directions

- do not take more than directed
- the smallest effective dose should be used
- do not take longer than 10 days, unless directed by a doctor (see Warnings)
- drink a full glass of water with each dose

adults and children 12 years and older | - take 1 tablet every 8 to 12 hours while symptoms last - for the first dose you may take 2 tablets within the first hour - do not exceed 2 tablets in any 8- to 12-hour period - do not exceed 3 tablets in a 24-hour period
children under 12 years | - ask a doctor

Other information

- each tablet contains:sodium 20 mg
- store at 20°-25°C (68°-77°F). Avoid high humidity and excessive heat above 40°C (104°F).
- retain carton for complete product information

Inactive ingredients

croscarmellose sodium, FD&C blue #2, macrogol, magnesium stearate, polyvinyl alcohol, povidone, pregelatinized starch, talc, titanium dioxide

Questions or comments?

1-844-292-1112

PRINCIPAL DISPLAY PANEL

Best Choice®

†Compare to the active ingredient in Aleve® Tablets

Naproxen Sodium

TABLETS, 220 mg

PAIN RELIEVER/FEVER REDUCER

(NSAID)

Strength to last 12 hours

Actual Size

50 TABLETS